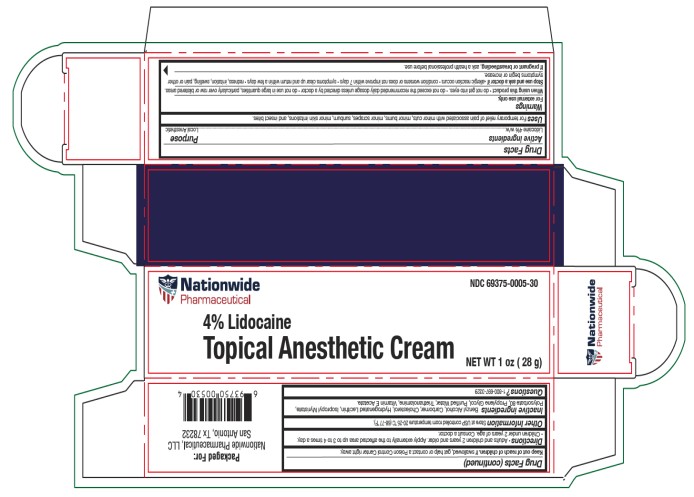 DRUG LABEL: Lidocaine Anesthetic Cream
NDC: 69375-005 | Form: CREAM
Manufacturer: Nationwide Pharmaceutical LLC
Category: otc | Type: HUMAN OTC DRUG LABEL
Date: 20250605

ACTIVE INGREDIENTS: LIDOCAINE 4 g/100 g
INACTIVE INGREDIENTS: BENZYL ALCOHOL; CARBOMER HOMOPOLYMER TYPE C (ALLYL PENTAERYTHRITOL CROSSLINKED); CHOLESTEROL; HYDROGENATED SOYBEAN LECITHIN; ISOPROPYL MYRISTATE; POLYSORBATE 80; TROLAMINE; .ALPHA.-TOCOPHEROL ACETATE, D-

Lidocaine Cream

Drug Facts

Active ingredients

Lidocaine 4% w/w

Purpose

Local Anesthetic

Uses

For temporary relief of pain associated with minor cuts, minor burns, minor scrapes, sunburn, minor skin irritations, and insect bites.

Warnings

For external use only.

When using this product

- do not get into eyes.
- do not exceed the recommended daily dosage unless directed by a doctor
- do not use in large quantities, particularly over raw or blistered areas.

Stop use and ask a doctor if

- allergic reaction occurs
- condition worsens or does not improve within 7 days
- symptoms clear up and return within a few days
- redness, irritation, swelling, pain or other symptoms begin or increase.

If pregnant or breastfeeding,

ask a health professional before use.

Keep out of reach of children.

If swallowed, get help or contact a Poison Control Center right away.

Directions

- Adults and children 2 years and older. Apply externally to the affected area up to 3 to 4 times a day.
- Children under 2 years of age. Consult a doctor.

Other Information

Store at USP controlled room temperature 20-25 °C (68-77 °F).

Inactive ingredients

Benzyl Alcohol, Carbomer, Cholesterol, Hydrogenated Lecithin, Isopropyl Myristate, Polysorbate 80, Propylene Glycol, Purified Water, Triethanolamine, Vitamin E Acetate.

Questions?

1-800-697-3329

PRINCIPAL DISPLAY PANEL - 28 g Tube Box

Nationwide
Pharmaceutical

NDC 69375-0005-30

4% Lidocaine
Topical Anesthetic Cream

NET WT 1 oz (28 g)